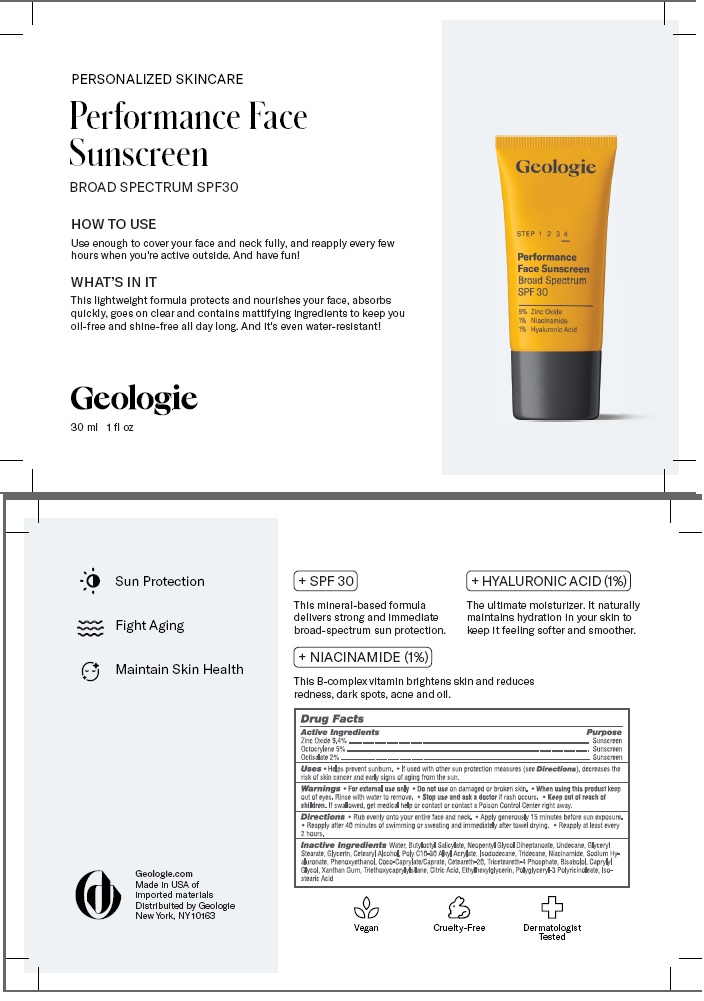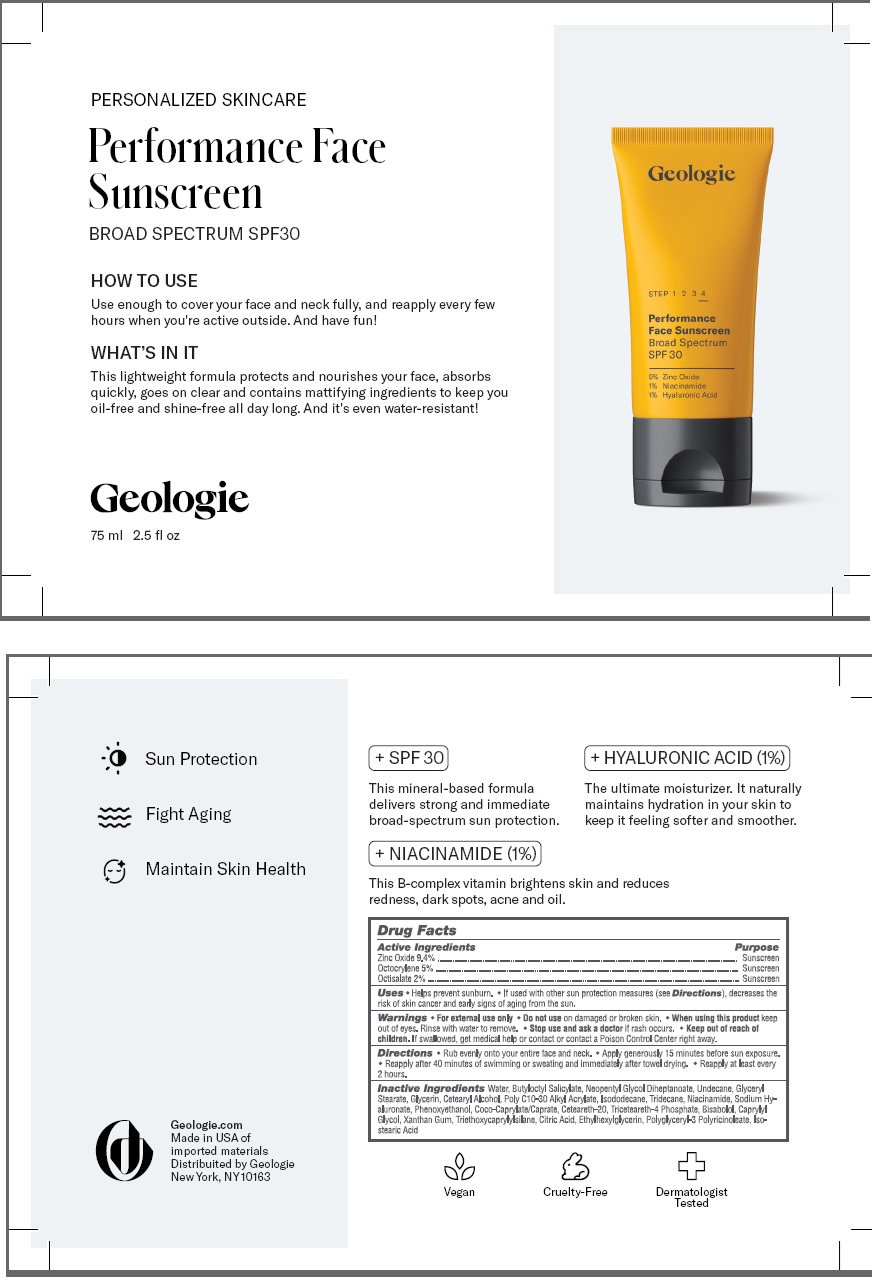 DRUG LABEL: Performance Face Sunscreen Broad Spectrum
NDC: 54111-188 | Form: CREAM
Manufacturer: Bentley Laboratories, LLC
Category: otc | Type: HUMAN OTC DRUG LABEL
Date: 20241206

ACTIVE INGREDIENTS: ZINC OXIDE 9.4 g/100 mL; OCTOCRYLENE 5.0 g/100 mL; OCTISALATE 2.0 g/100 mL
INACTIVE INGREDIENTS: WATER; BUTYLOCTYL SALICYLATE; NEOPENTYL GLYCOL DIHEPTANOATE; UNDECANE; GLYCERYL STEARATE; GLYCERIN; CETEARYL ALCOHOL; BEHENYL ACRYLATE POLYMER; ISODODECANE; TRIDECANE; NIACINAMIDE; SODIUM HYALURONATE; PHENOXYETHANOL; COCO-CAPRYLATE/CAPRATE; CETEARETH-20; TRICETEARETH-4 PHOSPHATE; BISABOLOL; CAPRYLYL GLYCOL; XANTHAN GUM; TRIETHOXYCAPRYLYLSILANE; CITRIC ACID; ETHYLHEXYLGLYCERIN; POLYGLYCERYL-3 PENTARICINOLEATE; ISOSTEARIC ACID

Geologie Performance Face Sunscreen Broad Spectrum SPF 30

DRUG FACTS

Active Ingredients

Zinc Oxide 9.4%

Octocrylene 5%

Octisalate 2%

Purpose

Zinc Oxide ......... Sunscreen

Octocrylene ....... Sunscreen

Octisalate .......... Sunscreen

INDICATIONS AND USAGE

Uses •Helps prevent sunburn • if used as directed with other sun protection measures (see Directions) decreases the
risk of skin cancer and early skin aging caused by the sun.

WARNINGS

Warnings • For external use only. • Do not use on damaged or broken skin. • When using this product keep

out of eyes. Rinse with water to remove. • Stop use and ask doctor if rash occurs.

KEEP OUT OF REACH OF CHILDREN

• Keep out of the reach of children. If swallowed get medical help

or contact a Poison Control center right away.

Directions

• Rub evenly into your rntire face and neck. • Apply generously liberally 15 minutes before sun exposure.
• Reapply after 40 minutes of swimming or sweating and immediately after towel drying. • Reapply at least every 2 hours

INACTIVE INGREDIENT

Inactive Ingredients Water, Butyloctyl Salicylate, Neopentyl Glycol Diheptanoate, Undecane, Glyceryl
Stearate, Glycerin, Cetearyl Alcohol, Poly C10-30 Alkyl Acrylate, Isododecane, Tridecane, Niacinamide, Sodium Hy-
aluronate, Phenoxyethanol, Coco-Caprylate/Caprate, Ceteareth-20, Triceteareth-4 Phosphate, Bisabolol, Caprylyl
Glycol, Xanthan Gum, Triethoxycaprylylsilane, Citric Acid, Ethylhexylglycerin, Polyglyceryl-3 Pentaricinoleate,
Isostearic Acid

Geologie Performance Face Sunscreen Broad Spectrum SPF 30

PERSONALIZED SKINCARE

Performance Face

Sunscreen

Broad Spectrum SPF30

Geologie

Geologie.com
Made in USA of
Imported Materials
Distributed by Geologie
New York, NY 10025

30 mL Tube

75 mL Tube

res